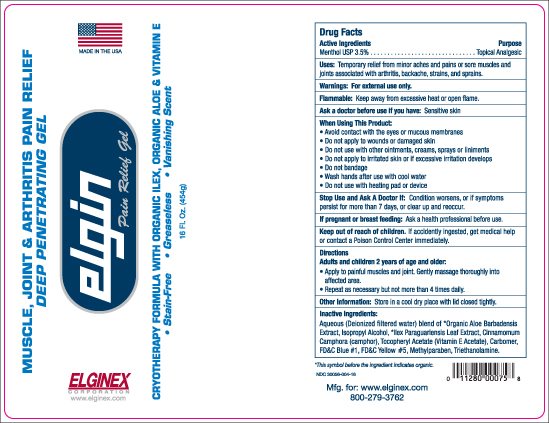 DRUG LABEL: Elgin Pain Relief
NDC: 30056-004 | Form: GEL
Manufacturer: Eco-Logics, Inc.
Category: otc | Type: HUMAN OTC DRUG LABEL
Date: 20251018

ACTIVE INGREDIENTS: MENTHOL 35 mg/1 g
INACTIVE INGREDIENTS: CAMPHOR (NATURAL); METHYLPARABEN; TROLAMINE; FD&C YELLOW NO. 5; ALOE VERA LEAF; ISOPROPYL ALCOHOL; ILEX PARAGUARIENSIS LEAF; ALPHA-TOCOPHEROL; FD&C BLUE NO. 1; WATER; CARBOMER HOMOPOLYMER TYPE C (ALLYL PENTAERYTHRITOL CROSSLINKED)

OTC-ACTIVE INGREDIENT SECTION

Active Ingedients Purpose

Menthol USP 3.5%................... Topical Analgesic

Purpose

Menthol USP 3.5% Topical Analgesic

Warnings

For external use only.

Directions:

Adults and children 2 years of age and older:

Apply to painful muscles and joints. Genthly massage throughly into affected area.

Repeat as necessary but not more than 4 times daily.

Ask a doctor before use if you have sensitive skin.

When using this product:

Avoid contact with the eyes or mucous membranes.

Do not apply to wounds or damaged skin.

Do not use with other ointments , creams, sprays or linaments.

Do not apply to irrated skin or excessive irration develops.

Do not bandage.

Wash hands after use with cool water.

Dop not use with heating pad or device.

Stop Use and ask a doctor if::

Stop use and ask a Dictor if: Condition worsens, or if symptoms persist for more than 7 days or clear up and reoccur.

If pregnant or breast feeding: Ask a health professional before use.

Keep out of reach of children. If accidenthly ingested get medical help or contact a Poison Control Center.

Inactive Ingredients:

Aqueous (Deionized filtered water) blend of certified * Organic Aloe Barbadensis Extract, Isopropyl Alcohol, *IlexParaguariensis leaf extract, Cinnamomum Camphora (camphor),Tocopheryl Avetate (Vitamin E Acetate), Carbomer, FD&C Blue #1, FD&C Yellow #5, Methylparaben, Triethanolamine.

Dosage and Administration

Directions:

Adults and children 2 years of age and older

Apply to painful muscles and joints. Genthly massage thoroughly into affected area.

Repeat as necessary but not more than 4 times daily.

Other information:

Other information: Stiore in a cool dry place with lid closed tightly.

USES:

Temporary relief from minor aches and pains of sore muscles and joints associated with arthritis, backache, strains, and sprains.